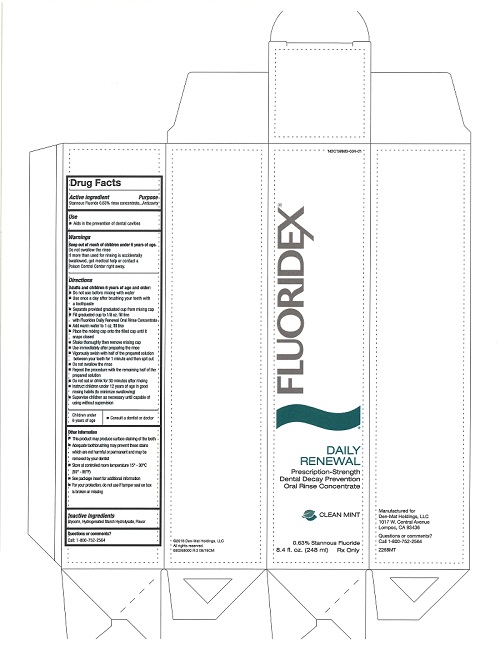 DRUG LABEL: Fluoridex
NDC: 59883-004 | Form: LIQUID
Manufacturer: DEN-MAT HOLDINGS, LLC
Category: otc | Type: HUMAN OTC DRUG LABEL
Date: 20231120

ACTIVE INGREDIENTS: STANNOUS FLUORIDE 1.53 mg/1 g
INACTIVE INGREDIENTS: GLYCERIN; HYDROGENATED STARCH HYDROLYSATE

Fluoridex - 0.63% Stannous Fluoride Rinse

Active ingredient

Stannous Fluoride 0.63% Rinse Concentrate

Purpose

Anticavity

Use

- Aids in the prevention of dental cavities

Warnings

Keep out of reach of children under 6 years of age.

If more than used for rinsing is accidentally swallowed, get medical help or contact a Poison Control Center right away

WARNINGS

Do not swallow the rinse

Directions

Adults and children 6 years of age and older:

- Do not use before mixing with water
- Use once a day after brushing your teeth with a toothpaste
- Separate provided graduated cup from the mixing cap
- Fill graduated cup to 1/8oz. fill line with Fluoridex Daily Renewal Oral Rinse Concentrate
- Add warm water to 1 oz. fill line
- Place the mixing cap onto the filled cap until it snaps closed
- Shake thoroughly then remove mixing cap
- Use immediately after preparing the rinse
- Vigorously swish with half of the prepared solution between your teeth for 1 minute and then spit out
- Do not swallow the rinse
- Repeat the procedure with the remaining half of the prepared solution
- Do not eat or drink for 30 minutes after rinising
- Instruct children under 12 years of age in good rinsing habits (to minimize swallowing)
- Supervise children as necessary until capable of using without supervision

Children under 6 years of age

- Consult a dentist or doctor

Other Information

- This product may produce surface staining of the teeth
- Adequatetoothbrushing may prevent these stains which are harmful or permanent and may be removed by your dentist
- Store at controlled room temperature 15º - 30ºC (59º - 86º F)
- See package insert for additional information
- For your protection, do not use if tamper seal on box is broken or missing

Inactive Ingredients

Glycerin, Hydrogenated Starch Hydrolysate, Flavor

Questions or comments?

Call: 1-800-752-2564

PACKAGE LABEL

NDC 59883-004-01

FLUORIDEX

DAILY

RENEWAL

Prescription-Strength

Dental Decay Prevention

Oral Rinse Concentrate

CLEAN MINT

0.63% Stannous Fluoride

8.4 fl. oz. (248 ml) Rx Only